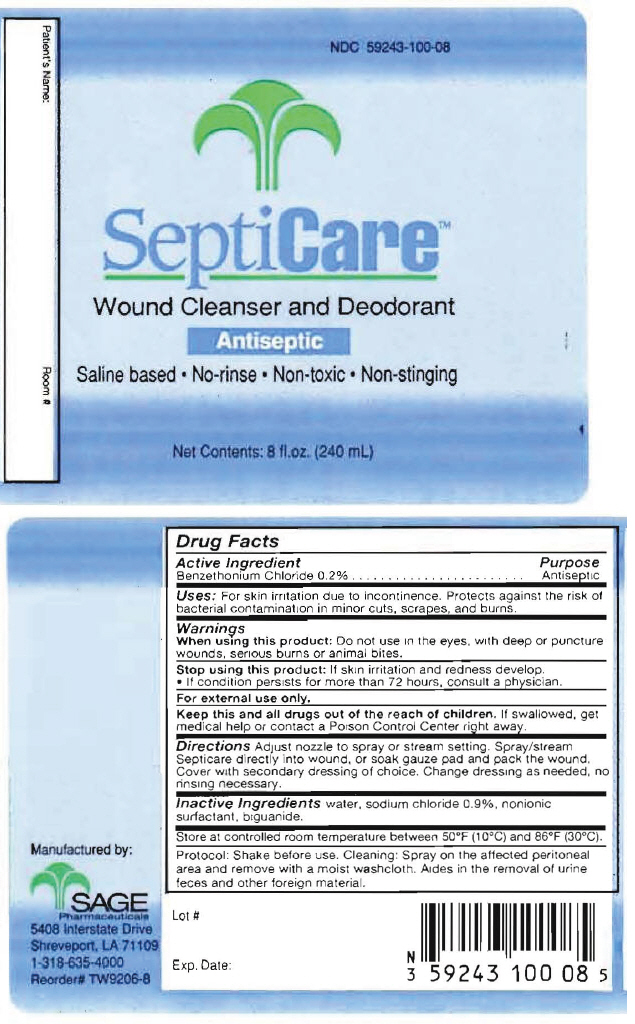 DRUG LABEL: Septicare
NDC: 59243-100 | Form: SOLUTION
Manufacturer: Sage Pharmaceuticals, Inc.
Category: otc | Type: HUMAN OTC DRUG LABEL
Date: 20130805

ACTIVE INGREDIENTS: BENZETHONIUM CHLORIDE 2 mg/1 mL
INACTIVE INGREDIENTS: SODIUM CHLORIDE 9 mg/1 mL; POLOXAMER 188; POLIHEXANIDE; WATER

Septicare™

Drug Facts

Active Ingredient

Benzethonium Chloride 0.2%

Purpose

Antiseptic

Uses

For skin irritation due to incontinence. Protects against the risk of bacterial contamination in minor cuts, scrapes, and burns.

Warnings

When using this product

Do not use in the eyes, with deep or puncture wounds, serious burns or animal bites.

Stop using this product

If skin irritation and redness develop.

- If condition persists for more than 72 hours, consult a physician.

For external use only.

KEEP OUT OF REACH OF CHILDREN

Keep this and all drugs out of the reach of children. If swallowed, get medical help or contact a Poison Control Center right away.

Directions

Adjust nozzle to spray or stream setting. Spray/stream Septicare directly into wound, or soak gauze pad and pack the wound. Cover with secondary dressing of choice. Change dressing as needed, no rinsing necessary.

Inactive Ingredients

water, sodium chloride 0.9%, nonionic surfactant, biguanide.

STORAGE AND HANDLING

Store at controlled room temperature between 50°F (10°C) and 86°F (30°C).

Protocol: Shake before use. Cleaning: Spray on the affected peritoneal area and remove with a moist washcloth. Aides in the removal of urine feces and other foreign material.

Manufactured by:
SAGE
PHARMACEUTICALS
5408 Interstate Drive
Shreveport, LA 71109

PRINCIPAL DISPLAY PANEL - 240 mL Bottle Label

NDC 59243-100-08

SeptiCare™

Wound Cleanser and Deodorant

Antiseptic

Saline based • No-rinse • Non-toxic • Non-stinging

Net Contents: 8 fl.oz. (240 mL)